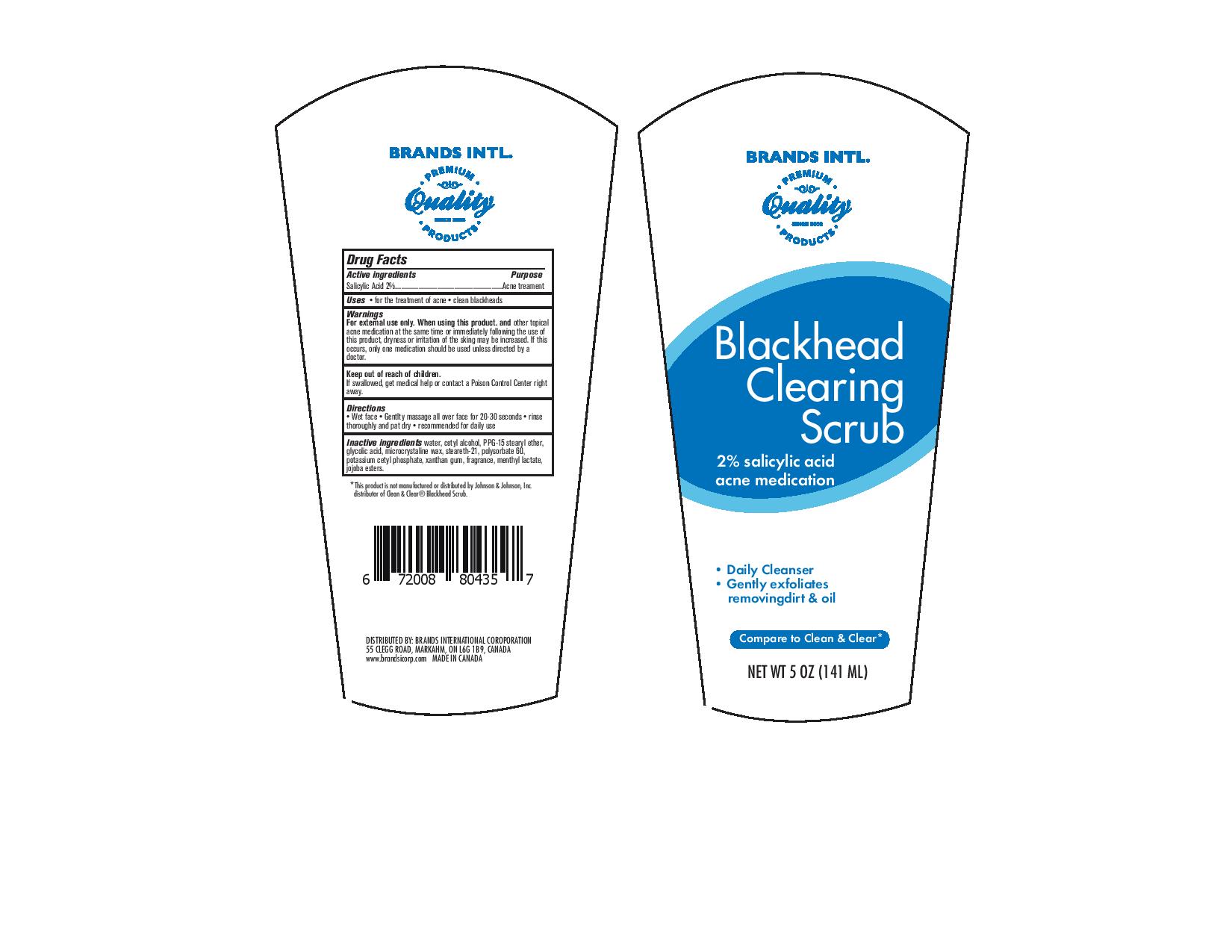 DRUG LABEL: Blackhead clearing scrub
NDC: 50157-204 | Form: RINSE
Manufacturer: Brands International Corp
Category: otc | Type: HUMAN OTC DRUG LABEL
Date: 20161023

ACTIVE INGREDIENTS: SALICYLIC ACID 0.2 mg/100 mg
INACTIVE INGREDIENTS: MICROCRYSTALLINE WAX; STEARETH-21; POLYSORBATE 60; POTASSIUM CETYL PHOSPHATE; XANTHAN GUM; MENTHYL LACTATE, (-)-; HYDROLYZED JOJOBA ESTERS (ACID FORM); PPG-15 STEARYL ETHER; GLYCOLIC ACID; WATER; CETYL ALCOHOL

Active Ingredient - Salicylic Acid 2%

Purpose - Acne Treatment

Uses

- for the treatment of acne
- clean blackheads

Warning

For external use only

When using this product and other topical acne medication at the same time or immediately following the use of this product, dryness or irritation of the skin may be increased. If this occurs, only one medication should be used unless directed by a doctor

Keep out of reach of children

If swallowed get medical help or contact a Poison Control Center right away

Directions

- Wet face
- gently massage all over face for 20-30 seconds
- rinse thoroughly and pat dry
- recommended for daily use

INACTIVE INGREDIENT

Water, Cetyl Alcohol, PPG-15 Stearyl Ether, Glycolic Acid, Microcrystalline wax, Steareth - 21, Polysorbate 60, potassium cetyl phosphate, xanthan gum, fragrance, menthyl lactate, jojoba esters